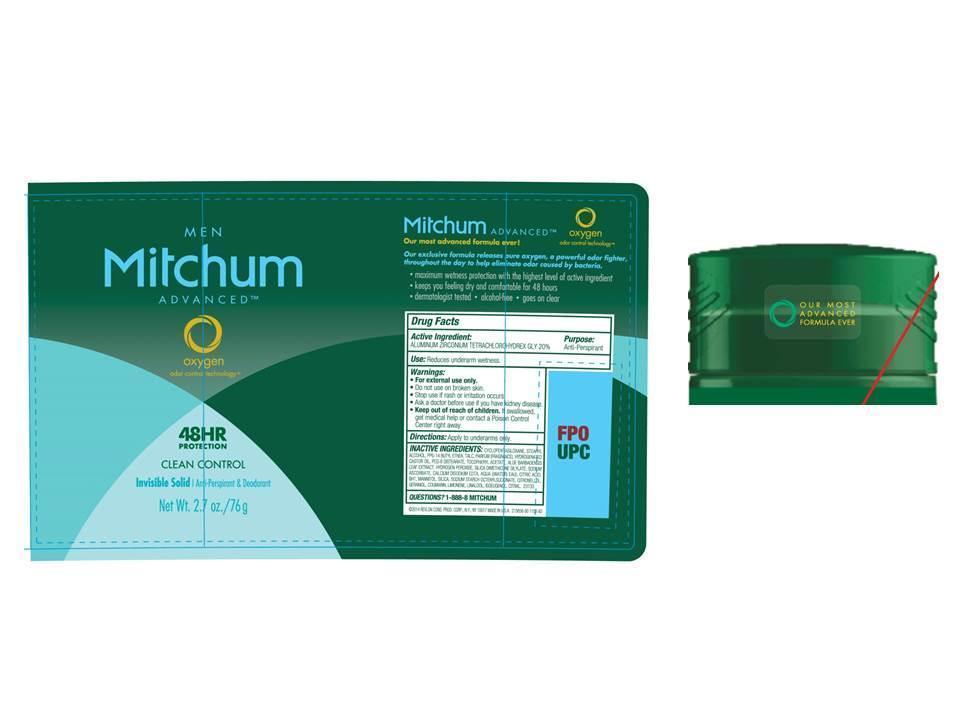 DRUG LABEL: Womens Mitchum Advanced Invisible Antiperspirant Deodorant
NDC: 10967-587 | Form: STICK
Manufacturer: Revlon Consumer Products Corp
Category: otc | Type: HUMAN OTC DRUG LABEL
Date: 20140130

ACTIVE INGREDIENTS: ALUMINUM ZIRCONIUM TETRACHLOROHYDREX GLY 0.20 g/1 g
INACTIVE INGREDIENTS: CYCLOMETHICONE 5; STEARYL ALCOHOL; ALKYL (C12-15) BENZOATE; HYDROGENATED CASTOR OIL; DIMETHICONE; TALC; PEG-8 DISTEARATE; .ALPHA.-TOCOPHEROL ACETATE; ALOE VERA LEAF; HYDROGEN PEROXIDE; LAURETH-23; SILICON DIOXIDE; .ALPHA.-HEXYLCINNAMALDEHYDE; LIMONENE, (+)-; ISOMETHYL-.ALPHA.-IONONE; COUMARIN; .BETA.-CITRONELLOL, (R)-; BENZYL BENZOATE

Womens Mitchum Advanced Invisible Solid Antiperspirant Deodorant (Pure Fresh)- 2.7 oz.

Drug Facts Active Ingredient

Aluminum zirconium tetrachlorohydrex gly 20%

Purpose

Antiperspirant

Use

- Reduces underarm wetness

Warnings:

For external use only.

Do not use on broken skin

Ask a doctor before use if you have kidney disease

Stop use if rash or irriation occurs

Keep out of reach of children.

If swallowed, get medical help or contact a Poison Control Center right away.

Directions

Apply to underarms only.

Inactive Ingredients

cyclopentasiloxane, stearyl alcohol, C12-15 Alkyl benzoate, hydrogenated castor oil, dimethicone, talc, parfum(fragrance), PEG-8 disterate, tocopheryl acetate, aloe barbadensis leaf extract, hydrogen peroxide, silica dimethicone silylate, laureth-23, silica, sodium starch octenylsuccinate, hexyl cinnamal, limonene, alpha-isomethyl ionone, coumarin, citronellol, benzyl benzoate

Questions

1-888-8-MITCHUM